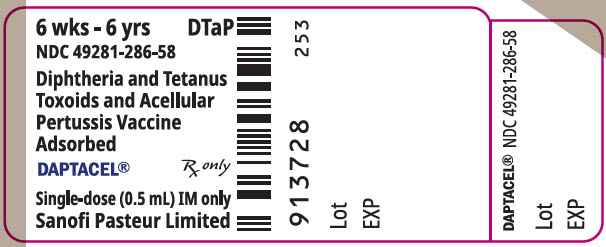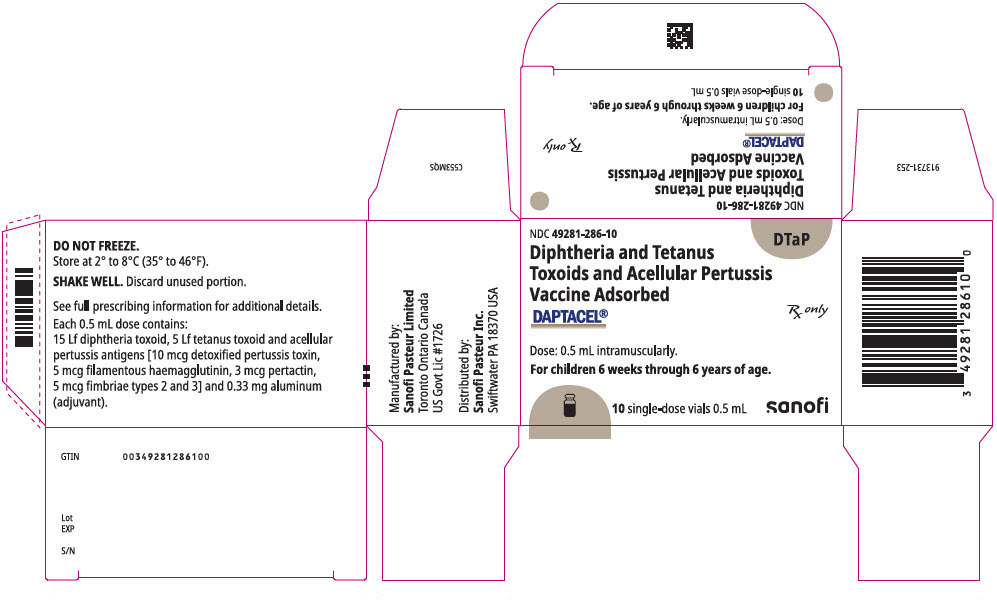 DRUG LABEL: DAPTACEL
NDC: 49281-286 | Form: INJECTION, SUSPENSION
Manufacturer: Sanofi Pasteur Inc.
Category: other | Type: VACCINE LABEL
Date: 20250312

ACTIVE INGREDIENTS: CORYNEBACTERIUM DIPHTHERIAE TOXOID ANTIGEN (FORMALDEHYDE INACTIVATED) 15 [Lf]/0.5 mL; CLOSTRIDIUM TETANI TOXOID ANTIGEN (FORMALDEHYDE INACTIVATED) 5 [Lf]/0.5 mL; BORDETELLA PERTUSSIS TOXOID ANTIGEN (GLUTARALDEHYDE INACTIVATED) 10 ug/0.5 mL; BORDETELLA PERTUSSIS FILAMENTOUS HEMAGGLUTININ ANTIGEN (FORMALDEHYDE INACTIVATED) 5 ug/0.5 mL; BORDETELLA PERTUSSIS PERTACTIN ANTIGEN 3 ug/0.5 mL; BORDETELLA PERTUSSIS FIMBRIAE 2/3 ANTIGEN 5 ug/0.5 mL
INACTIVE INGREDIENTS: ALUMINUM PHOSPHATE 1.5 mg/0.5 mL; FORMALDEHYDE 5 ug/0.5 mL; GLUTARAL 50 ng/0.5 mL; PHENOXYETHANOL 3.3 mg/0.5 mL; WATER

HIGHLIGHTS OF PRESCRIBING INFORMATION

These highlights do not include all the information needed to use DAPTACEL safely and effectively. See full prescribing information for DAPTACEL.
DAPTACEL (Diphtheria and Tetanus Toxoids and Acellular Pertussis Vaccine Adsorbed)
Suspension for Intramuscular Injection
Initial U.S. Approval: 2002

1 INDICATIONS AND USAGE

- DAPTACEL is a vaccine indicated for active immunization against diphtheria, tetanus and pertussis as a five-dose series in infants and children 6 weeks through 6 years of age (prior to 7th birthday). (1)

2 DOSAGE AND ADMINISTRATION

- The five dose immunization series consists of a 0.5 mL intramuscular injection administered at 2, 4, 6 and 15-20 months of age, and at 4-6 years of age. (2.1, 2.2)

3 DOSAGE FORMS AND STRENGTHS

- Suspension for injection, supplied in single-dose (0.5 mL) vials (3)

4 CONTRAINDICATIONS

- Severe allergic reaction (e.g., anaphylaxis) after a previous dose of any diphtheria toxoid, tetanus toxoid, or pertussis-containing vaccine, or any component of DAPTACEL. (4.1)
- Encephalopathy within 7 days of a previous pertussis-containing vaccine with no other identifiable cause. (4.2)
- Progressive neurologic disorder until a treatment regimen has been established and the condition has stabilized. (4.3)

5 WARNINGS AND PRECAUTIONS

- Carefully consider benefits and risks before administering DAPTACEL to persons with a history of:
  - fever ≥40.5°C (105°F), hypotonic-hyporesponsive episode (HHE) or persistent, inconsolable crying lasting ≥3 hours within 48 hours after a previous pertussis-containing vaccine. (5.2)
  - seizures within 3 days after a previous pertussis-containing vaccine. (5.2)
  - If Guillain-Barré syndrome occurred within 6 weeks of receipt of a prior vaccine containing tetanus toxoid, the risk for Guillain-Barré syndrome may be increased following DAPTACEL. (5.3)
- For infants and children with a history of previous seizures, an antipyretic may be administered (in the dosage recommended in its prescribing information) at the time of vaccination with DAPTACEL and for the next 24 hours. (5.4)
- Apnea following intramuscular vaccination has been observed in some infants born prematurely. The decision about when to administer an intramuscular vaccine, including DAPTACEL, to an infant born prematurely should be based on consideration of the individual infant's medical status and the potential benefits and possible risks of vaccination. (5.7)

6 ADVERSE REACTIONS

- Rates of adverse reactions varied by dose number, with systemic reactions most frequent following doses 1-3 and injection site reactions most frequent following doses 4 and 5. Systemic reactions that occurred in >50% of subjects following any dose included fussiness/irritability, inconsolable crying, and decreased activity/lethargy. Fever ≥38.0°C occurred in 6-16% of US subjects, depending on dose number. Injection site reactions that occurred in >30% of subjects following any dose included tenderness, redness and increase in arm circumference. (6.1)

To report SUSPECTED ADVERSE REACTIONS, contact Sanofi Pasteur Inc., at 1-800-822-2463 (1-800-VACCINE) or VAERS at 1-800-822-7967 and http://vaers.hhs.gov.

7 DRUG INTERACTIONS

- In cases where DAPTACEL and Menactra are to be administered to children 4 through 6 years of age, the two vaccines should be administered concomitantly or Menactra should be administered prior to DAPTACEL. Administration of Menactra one month after DAPTACEL has been shown to reduce meningococcal antibody responses to Menactra. (7.1)
- Do not mix with any other vaccine in the same syringe or vial. (7.1)
- Immunosuppressive therapies may reduce the immune response to DAPTACEL. (7.2)

FULL PRESCRIBING INFORMATION

1 INDICATIONS AND USAGE

DAPTACEL® is a vaccine indicated for active immunization against diphtheria, tetanus and pertussis as a five-dose series in infants and children 6 weeks through 6 years of age (prior to seventh birthday).

2 DOSAGE AND ADMINISTRATION

For intramuscular injection only.

2.1 Immunization Series

DAPTACEL is to be administered as a 5 dose series at 2, 4 and 6 months of age (at intervals of 6-8 weeks), at 15-20 months of age and at 4-6 years of age. The first dose may be given as early as 6 weeks of age. Four doses of DAPTACEL constitute a primary immunization course for pertussis. The fifth dose is a booster for pertussis immunization. Three doses of DAPTACEL constitute a primary immunization course for diphtheria and tetanus. The fourth and fifth doses are boosters for diphtheria and tetanus immunization. [See Clinical Studies (14.1, 14.2, 14.3).]

Mixed Sequences of DAPTACEL and other DTaP-containing Vaccines

DAPTACEL contains the same pertussis antigens, manufactured by the same process, as Pentacel® [Diphtheria and Tetanus Toxoids and Acellular Pertussis Adsorbed, Inactivated Poliovirus and Haemophilus b Conjugate (Tetanus Toxoid Conjugate) vaccine] and VAXELIS (Diphtheria and Tetanus Toxoids and Acellular Pertussis, Inactivated Poliovirus, Haemophilus b Conjugate and Hepatitis B Vaccine). Pentacel and VAXELIS contain twice the amount of detoxified pertussis toxin (PT) and four times the amount of filamentous hemagglutinin (FHA) as DAPTACEL.

DAPTACEL may be used as any of the doses in a 5-dose DTaP series initiated with Pentacel or VAXELIS.

Data are not available on the safety and effectiveness of using mixed sequences of DAPTACEL and DTaP-containing vaccines from different manufacturers for successive doses of the DTaP vaccination series.

2.2 Administration

Parenteral drug products should be inspected visually for particulate matter and discoloration prior to administration, whenever solution and container permit. If either of these conditions exist, the product should not be administered.

Just before use, shake the vial well, until a uniform, white, cloudy suspension results.

Withdraw and administer a single 0.5 mL dose of DAPTACEL intramuscularly. Discard unused portion. Use a separate sterile needle and syringe for each injection. Changing needles between withdrawing the vaccine from the vial and injecting it into a recipient is not necessary unless the needle has been damaged or contaminated. In infants younger than 1 year, the anterolateral aspect of the thigh provides the largest muscle and is the preferred site of injection. In older children, the deltoid muscle is usually large enough for injection. The vaccine should not be injected into the gluteal area or areas where there may be a major nerve trunk.

Do not administer this product intravenously or subcutaneously.

DAPTACEL should not be combined through reconstitution or mixed with any other vaccine.

3 DOSAGE FORMS AND STRENGTHS

DAPTACEL is a suspension for injection in 0.5 mL single-dose vials. See Description (11) for a complete listing of ingredients.

4 CONTRAINDICATIONS

4.1 Hypersensitivity

A severe allergic reaction (e.g., anaphylaxis) after a previous dose of DAPTACEL or any other tetanus toxoid, diphtheria toxoid, or pertussis-containing vaccine, or any other component of this vaccine is a contraindication to administration of DAPTACEL. [See Description (11).] Because of uncertainty as to which component of the vaccine may be responsible, none of the components should be administered. Alternatively, such individuals may be referred to an allergist for evaluation if further immunizations are to be considered.

4.2 Encephalopathy

Encephalopathy (e.g., coma, decreased level of consciousness, prolonged seizures) within 7 days of a previous dose of a pertussis containing vaccine that is not attributable to another identifiable cause is a contraindication to administration of any pertussis-containing vaccine, including DAPTACEL.

4.3 Progressive Neurologic Disorder

Progressive neurologic disorder, including infantile spasms, uncontrolled epilepsy, or progressive encephalopathy is a contraindication to administration of any pertussis-containing vaccine, including DAPTACEL. Pertussis vaccine should not be administered to individuals with such conditions until a treatment regimen has been established and the condition has stabilized.

5 WARNINGS AND PRECAUTIONS

5.1 Management of Acute Allergic Reactions

Epinephrine hydrochloride solution (1:1,000) and other appropriate agents and equipment must be available for immediate use in case an anaphylactic or acute hypersensitivity reaction occurs.

5.2 Adverse Reactions Following Prior Pertussis Vaccination

If any of the following events occur within the specified period after administration of a whole-cell pertussis vaccine or a vaccine containing an acellular pertussis component, the decision to administer DAPTACEL should be based on careful consideration of potential benefits and possible risks. [See Dosage and Administration (2.1).]

- Temperature of ≥40.5°C (105°F) within 48 hours, not attributable to another identifiable cause.
- Collapse or shock-like state (hypotonic-hyporesponsive episode [HHE]) within 48 hours.
- Persistent, inconsolable crying lasting ≥3 hours within 48 hours.
- Seizures with or without fever within 3 days.

5.3 Guillain-Barré Syndrome and Brachial Neuritis

A review by the Institute of Medicine found evidence for a causal relation between tetanus toxoid and both brachial neuritis and Guillain-Barré syndrome. (1) If Guillain-Barré syndrome occurred within 6 weeks of receipt of a prior vaccine containing tetanus toxoid, the risk for Guillain-Barré syndrome may be increased following DAPTACEL.

5.4 Infants and Children with a History of Previous Seizures

For infants or children with a history of previous seizures, an appropriate antipyretic may be administered (in the dosage recommended in its prescribing information) at the time of vaccination with a vaccine containing an acellular pertussis component (including DAPTACEL) and for the following 24 hours, to reduce the possibility of post-vaccination fever.

5.5 Limitations of Vaccine Effectiveness

Vaccination with DAPTACEL may not protect all individuals.

5.6 Altered Immunocompetence

If DAPTACEL is administered to immunocompromised persons, including persons receiving immunosuppressive therapy, the expected immune response may not be obtained. [See Immunosuppressive Treatments (7.2).]

5.7 Apnea in Premature Infants

Apnea following intramuscular vaccination has been observed in some infants born prematurely. The decision about when to administer an intramuscular vaccine, including DAPTACEL, to an infant born prematurely should be based on consideration of the individual infant's medical status and the potential benefits and possible risks of vaccination.

5.8 Syncope

Syncope (fainting) has been reported following vaccination with DAPTACEL. Procedures should be in place to avoid injury from fainting.

6 ADVERSE REACTIONS

6.1 Data from Clinical Studies

Because clinical trials are conducted under widely varying conditions, adverse reaction rates observed in the clinical trials of a vaccine cannot be directly compared to rates in the clinical trials of another vaccine and may not reflect the rates observed in practice. The adverse reaction information from clinical trials does, however, provide a basis for identifying the adverse events that appear to be related to vaccine use and for approximating rates of those events.

Approximately 18,000 doses of DAPTACEL have been administered to infants and children in 9 clinical studies. Of these, 3 doses of DAPTACEL were administered to 4,998 children, 4 doses of DAPTACEL were administered to 1,725 children, and 5 doses of DAPTACEL were administered to 485 children. A total of 989 children received 1 dose of DAPTACEL following 4 prior doses of Pentacel.

In a randomized, double-blinded pertussis vaccine efficacy trial, the Sweden I Efficacy Trial, conducted in Sweden during 1992-1995, the safety of DAPTACEL was compared with DT and a whole-cell pertussis DTP vaccine. A standard diary card was kept for 14 days after each dose and follow-up telephone calls were made 1 and 14 days after each injection. Telephone calls were made monthly to monitor the occurrence of severe events and/or hospitalizations for the 2 months after the last injection. There were fewer of the solicited common local and systemic reactions following DAPTACEL than following the whole-cell pertussis DTP vaccine. As shown in Table 1, the 2,587 infants who received DAPTACEL at 2, 4 and 6 months of age had similar rates of reactions within 24 hours as recipients of DT and significantly lower rates than infants receiving whole-cell pertussis DTP.

Table 1: Percentage of Infants from Sweden I Efficacy Trial with Local or Systemic Reactions within 24 Hours Post-Dose 1, 2 and 3 of DAPTACEL compared with DT and Whole-Cell Pertussis DTP Vaccines
Event | Dose 1 (2 MONTHS) DAPTACEL N = 2,587 | Dose 1 (2 MONTHS) DT N = 2,574 | Dose 1 (2 MONTHS) DTP N = 2,102 | Dose 2 (4 MONTHS) DAPTACEL N = 2,563 | Dose 2 (4 MONTHS) DT N = 2,555 | Dose 2 (4 MONTHS) DTP N = 2,040 | Dose 3 (6 MONTHS) DAPTACEL N = 2,549 | Dose 3 (6 MONTHS) DT N = 2,538 | Dose 3 (6 MONTHS) DTP N = 2,001
Local
Tenderness (Any) | 8.0 [p<0.001: DAPTACEL versus whole-cell pertussis DTP] | 8.4 | 59.5 | 10.1 | 10.3 | 60.2 | 10.8 | 10.0 | 50.0
Redness ≥2 cm | 0.3 | 0.3 | 6.0 | 1.0 | 0.8 | 5.1 | 3.7 | 2.4 | 6.4
Swelling ≥2 cm | 0.9 | 0.7 | 10.6 | 1.6 | 2.0 | 10.0 | 6.3 [p<0.0001: DAPTACEL versus DT] | 3.9 | 10.5
Systemic
Fever [Rectal temperature] ≥38°C (100.4°F) | 7.8 | 7.6 | 72.3 | 19.1 | 18.4 | 74.3 | 23.6 | 22.1 | 65.1
Fretfulness [Statistical comparisons were not made for this variable] | 32.3 | 33.0 | 82.1 | 39.6 | 39.8 | 85.4 | 35.9 | 37.7 | 73.0
Anorexia | 11.2 | 10.3 | 39.2 | 9.1 | 8.1 | 25.6 | 8.4 | 7.7 | 17.5
Drowsiness | 32.7 | 32.0 | 56.9 | 25.9 | 25.6 | 50.6 | 18.9 | 20.6 | 37.6
Crying ≥1 hour | 1.7 | 1.6 | 11.8 | 2.5 | 2.7 | 9.3 | 1.2 | 1.0 | 3.3
Vomiting | 6.9 | 6.3 | 9.5 | 5.2 [p<0.003: DAPTACEL versus whole-cell pertussis DTP] | 5.8 | 7.4 | 4.3 | 5.2 | 5.5
DT: Swedish National Biologics Laboratories
DTP: whole-cell pertussis DTP, Sanofi Pasteur Inc.
N = Number of evaluable subjects

The incidence of serious and less common selected systemic events in the Sweden I Efficacy Trial is summarized in Table 2.

Table 2: Selected Systemic Events: Rates Per 1,000 Doses after Vaccination at 2, 4 and 6 Months of Age in Sweden I Efficacy Trial
EVENT | Dose 1 (2 MONTHS) DAPTACEL N = 2,587 | Dose 1 (2 MONTHS) DT N = 2,574 | Dose 1 (2 MONTHS) DTP N = 2,102 | Dose 2 (4 MONTHS) DAPTACEL N = 2,565 | Dose 2 (4 MONTHS) DT N = 2556 | Dose 2 (4 MONTHS) DTP N = 2,040 | Dose 3 (6 MONTHS) DAPTACEL N = 2,551 | Dose 3 (6 MONTHS) DT N = 2,539 | Dose 3 (6 MONTHS) DTP N = 2,002
Rectal temperature ≥40°C (104°F) within 48 hours of vaccination | 0.39 | 0.78 | 3.33 | 0 | 0.78 | 3.43 | 0.39 | 1.18 | 6.99
Hypotonic-hypo-responsive episode within 24 hours of vaccination | 0 | 0 | 1.9 | 0 | 0 | 0.49 | 0.39 | 0 | 0
Persistent crying ≥3 hours within 24 hours of vaccination | 1.16 | 0 | 8.09 | 0.39 | 0.39 | 1.96 | 0 | 0 | 1.0
Seizures within 72 hours of vaccination | 0 | 0.39 | 0 | 0 | 0.39 | 0.49 | 0 | 0.39 | 0
DT: Swedish National Biologics Laboratories
DTP: whole-cell pertussis DTP, Sanofi Pasteur Inc.
N = Number of evaluable subjects

In the Sweden I Efficacy Trial, one case of whole limb swelling and generalized symptoms, with resolution within 24 hours, was observed following dose 2 of DAPTACEL. No episodes of anaphylaxis or encephalopathy were observed. No seizures were reported within 3 days of vaccination with DAPTACEL. Over the entire study period, 6 seizures were reported in the DAPTACEL group, 9 in the DT group and 3 in the whole-cell pertussis DTP group, for overall rates of 2.3, 3.5 and 1.4 per 1,000 vaccinees, respectively. One case of infantile spasms was reported in the DAPTACEL group. There were no instances of invasive bacterial infection or death.

In a US study, children received 4 doses of DAPTACEL at 2, 4, 6 and 15-17 months of age. A total of 1,454 children received DAPTACEL and were included in the safety analyses. Of these, 51.7% were female, 77.2% Caucasian, 6.3% Black, 6.5% Hispanic, 0.9% Asian and 9.1% other races. The use of DAPTACEL as a fifth dose of DTaP vaccine was evaluated in 2 subsequent US clinical studies. In one study, a total of 485 children received DAPTACEL at 4-6 years of age following 4 prior doses of DAPTACEL in infancy (DAPTACEL-primed). In a separate study, a total of 989 children received DAPTACEL at 4-6 years of age following 4 prior doses of Pentacel in infancy (Pentacel-primed). The children included in these fifth dose studies were non-random subsets of participants from previous DAPTACEL or Pentacel studies. The subsets were representative of all children who received 4 doses of DAPTACEL or Pentacel in the earlier studies with regard to frequencies of solicited local and systemic adverse events following the fourth dose.

In the US 4-dose DAPTACEL study, at 2, 4, and 6 months of age, DAPTACEL was administered concomitantly with Haemophilus influenzae type b (Hib) conjugate vaccine (tetanus toxoid conjugate) (Sanofi Pasteur SA), inactivated poliovirus vaccine (IPV) (Sanofi Pasteur SA), and 7-valent pneumococcal conjugate vaccine (Wyeth Pharmaceuticals Inc.). Infants had received the first dose of hepatitis B vaccine at 0 months of age. At 2 and 6 months of age, hepatitis B vaccine (recombinant) (Merck & Co., Inc.) was also administered concomitantly with DAPTACEL. Based on random assignment, the fourth dose of DAPTACEL was administered either alone; concomitantly with Hib conjugate (tetanus toxoid conjugate) vaccine; or concomitantly with Hib conjugate (tetanus toxoid conjugate) vaccine, 7-valent pneumococcal conjugate vaccine, measles, mumps, rubella (MMR) vaccine (Merck & Co., Inc.), and varicella vaccine (Merck & Co., Inc.). In the fifth dose studies, DAPTACEL was administered concomitantly with IPV (all DAPTACEL-primed subjects and 47% of Pentacel-primed subjects) and MMR vaccine.

In the US studies, the occurrence of solicited local and systemic adverse events listed in Table 3 was recorded daily by parents or guardians for Days 0-7 following vaccination. For Days 0 and 1 following the first three doses of DAPTACEL, signs and symptoms of HHE also were solicited. Periodic telephone calls were made to inquire about adverse events. Serious adverse events were monitored during the three studies, through 6 months following the last dose of DAPTACEL.

The incidence and severity of selected solicited local and systemic adverse events that occurred within 3 days following each dose of DAPTACEL are shown in Table 3. The incidence of redness, tenderness and swelling at the DAPTACEL injection site increased with the fourth and fifth doses, with the highest rates reported after the fifth dose. The incidence of redness, tenderness and swelling at the DAPTACEL injection site was similarly increased when DAPTACEL was given as a fifth dose of DTaP vaccine in Pentacel-primed children.

Table 3: Number (Percentage) of Children from US Studies with Selected Solicited Local and Systemic Adverse Events by Severity Occurring Between 0 to 3 Days after Each Dose of DAPTACEL
 | Dose 1 [In one US study, children received four doses of DAPTACEL. A non-random subset of these children received a fifth dose of DAPTACEL in a subsequent study. A non-random subset of children previously vaccinated with 4 doses of Pentacel in previous clinical studies received a dose of DAPTACEL at 4–6 years of age as the fifth dose of DTaP vaccine in another clinical study.] N = 1390–1406 % | Dose 2 N = 1346–1360 % | Dose 3 N = 1301–1312 % | Dose 4 N = 1118–1144 % | Dose 5 DAPTACEL-primed N = 473–481 % | Dose 5 Pentacel-primed N = 936–981 %
Injection Site Reactions (DAPTACEL injection site)
Redness
>5 mm | 6.2 | 7.1 | 9.6 | 17.3 | 35.8 | 20.2
25 – 50 mm | 0.6 | 0.5 | 1.9 | 6.3 | 10.4 | 6.8
>50 mm | 0.4 | 0.1 | 0.0 | 3.1 | 15.8 | 6.6
Swelling
>5 mm | 4.0 | 4.0 | 6.5 | 11.7 | 23.9 | 12.0
25 – 50 mm | 1.2 | 0.6 | 1.0 | 3.2 | 5.8 | 4.1
>50 mm | 0.4 | 0.1 | 0.1 | 1.6 | 7.7 | 2.9
Tenderness [Doses 1–4 - Moderate: subject cries when site is touched; Severe: subject cries when leg or arm is moved. Dose 5 - Moderate: interfered with activities, but did not require medical care or absenteeism; Severe: incapacitating, unable to perform usual activities, may have/or required medical care or absenteeism.]
Any | 48.8 | 38.2 | 40.9 | 49.5 | 61.5 | 50.0
Moderate | 16.5 | 9.9 | 10.6 | 12.3 | 11.2 | 7.4
Severe | 4.1 | 2.3 | 1.7 | 2.2 | 1.7 | 0.3
Increase in Arm Circumference [The circumference of the DAPTACEL-injected arm at the level of the axilla was monitored following the fourth and fifth doses only. Increase in arm circumference was calculated by subtracting the baseline circumference pre-vaccination (Day 0) from the circumference post-vaccination.]
>5 mm | - | - | - | 30.1 | 38.3 | 28.6
20 – 40 mm | - | - | - | 7.0 | 14.0 | 7.6
>40 mm | - | - | - | 0.4 | 1.5 | 1.2
Interference with Normal Activity of the Arm [Moderate: decreased use of arm, but did not require medical care or absenteeism; Severe: incapacitating, refusal to move arm, may have/or required medical care or absenteeism.]
Any | - | - | - | - | 20.4 | 8.8
Moderate | - | - | - | - | 5.6 | 1.7
Severe | - | - | - | - | 0.4 | 0.0
Systemic Reactions
Fever [For Doses 1–3, 53.7% of temperatures were measured rectally, 45.1% were measured axillary, 1.0% were measured orally, and 0.1% were measured by an unspecified route. For Dose 4, 35.7% of temperatures were measured rectally, 62.3% were measured axillary, 1.5% were measured orally, and 0.5% were measured by an unspecified route. For Dose 5 in DAPTACEL-primed children, 0.2% of temperatures were measured rectally, 11.3% were measured axillary, and 88.4% were measured orally. For Dose 5 in Pentacel-primed children, 0.2% of temperatures were measured rectally, 0.5% were measured tympanically, 17% were measured axillary, and 81.7% were measured orally. Fever is based upon actual temperatures recorded with no adjustments to the measurement for route.]
≥38.0°C | 9.3 | 16.1 | 15.8 | 10.5 | 6.1 | 4.6
>38.5–39.5°C | 1.5 | 3.9 | 4.8 | 2.7 | 2.1 | 2.0
>39.5°C | 0.1 | 0.4 | 0.3 | 0.7 | 0.2 | 0.2
Decreased Activity/Lethargy [Dose 1–4 - Moderate: interferes with and limits daily activity, less interactive; Severe: disabling (not interested in usual daily activity, subject cannot be coaxed to interact with caregiver). Dose 5 - Moderate: interfered with activities, but did not require medical care or absenteeism; Severe: incapacitating, unable to perform usual activities, may have/or required medical care or absenteeism.]
Any | 51.1 | 37.4 | 33.2 | 25.3 | 21.0 | 12.6
Moderate | 23.0 | 14.4 | 12.1 | 8.2 | 5.8 | 3.6
Severe | 1.2 | 1.4 | 0.6 | 1.0 | 0.8 | 0.4
Inconsolable Crying [Doses 1–4 - Moderate: 1 to 3 hours inconsolable crying; Severe: >3 hours inconsolable crying. Dose 5 - Moderate: interfered with activities, but did not require medical care or absenteeism; Severe: incapacitating, unable to perform usual activities, may have/or required medical care or absenteeism.]
Any | 58.5 | 51.4 | 47.9 | 37.1 | 14.1 | 7.2
Moderate | 14.2 | 12.6 | 10.8 | 7.7 | 3.5 | 1.9
Severe | 2.2 | 3.4 | 1.4 | 1.5 | 0.4 | 0.3
Fussiness/Irritability [Doses 1–4 - Moderate: Irritability for 1 to 3 hours; Severe: irritability for >3 hours. Dose 5 - Moderate: interfered with activities, but did not require medical care or absenteeism; Severe: incapacitating, unable to perform usual activities, may have/or required medical care or absenteeism.]
Any | 75.8 | 70.7 | 67.1 | 54.4 | 34.9 | 22.9
Moderate | 27.7 | 25.0 | 22.0 | 16.3 | 7.5 | 5.3
Severe | 5.6 | 5.5 | 4.3 | 3.9 | 0.4 | 0.5

In the US study in which children received 4 doses of DAPTACEL, of 1,454 subjects who received DAPTACEL, 5 (0.3%) subjects experienced a seizure within 60 days following any dose of DAPTACEL. One seizure occurred within 7 days post-vaccination: an infant who experienced an afebrile seizure with apnea on the day of the first vaccination. Three other cases of seizures occurred between 8 and 30 days post-vaccination. Of the seizures that occurred within 60 days post-vaccination, 3 were associated with fever. In this study, there were no reported cases of HHE following DAPTACEL. There was one death due to aspiration 222 days post-vaccination in a subject with ependymoma. Within 30 days following any dose of DAPTACEL, 57 (3.9%) subjects reported at least one serious adverse event. During this period, the most frequently reported serious adverse event was bronchiolitis, reported in 28 (1.9%) subjects. Other serious adverse events that occurred within 30 days following DAPTACEL include three cases of pneumonia, two cases of meningitis and one case each of sepsis, pertussis (post-dose 1), irritability and unresponsiveness.

In the US study in which DAPTACEL was administered as a fifth DTaP dose in DAPTACEL-primed subjects, within 30 days following the fifth consecutive dose of DAPTACEL, 1 (0.2%) subject reported 2 serious adverse events (bronchospasm and hypoxia). In the US study in which DAPTACEL was administered as a fifth DTaP dose in Pentacel-primed subjects, within 30 days following DAPTACEL, 4 (0.4%) subjects reported one or more serious adverse events (asthma and pneumonia; idiopathic thrombocytopenic purpura; vomiting; cellulitis not at the injection site). In these two studies, there were no reports of seizures within 30 days following DAPTACEL in either the DAPTACEL-primed subjects or Pentacel-primed subjects.

In another study (Sweden II Efficacy Trial), 3 DTaP vaccines and a whole-cell pertussis DTP vaccine, none of which are licensed in the US, were evaluated to assess relative safety and efficacy. This study included HCPDT, a vaccine made of the same components as DAPTACEL but containing twice the amount of detoxified PT and four times the amount of FHA (20 mcg detoxified PT and 20 mcg FHA). HHE was observed following 29 (0.047%) of 61,220 doses of HCPDT; 16 (0.026%) of 61,219 doses of an acellular pertussis vaccine made by another manufacturer; and 34 (0.056%) of 60,792 doses of a whole-cell pertussis DTP vaccine. There were 4 additional cases of HHE in other studies using HCPDT vaccine for an overall rate of 33 (0.047%) in 69,525 doses.

In a randomized, parallel-group, US multi-center clinical trial conducted in children 4 through 6 years of age, DAPTACEL was administered as follows: concomitantly with IPV (Sanofi Pasteur SA) followed 30 days later by Menactra® [Meningococcal (Groups A, C, Y and W-135) Polysaccharide Diphtheria Toxoid Conjugate vaccine, Sanofi Pasteur Inc.] [Group A]; concomitantly with Menactra followed 30 days later by IPV [Group B]; or 30 days after concomitant administration of Menactra and IPV [Group C]. Solicited injection site and systemic reactions were recorded in a diary card for 7 consecutive days after each vaccination. For all study groups, the most frequently reported solicited local reaction at the DAPTACEL injection site was pain: 71.7%, 69.4% and 52.1% of subjects in Groups A, B and C, respectively. For all study groups, the most frequently reported systemic reaction after DAPTACEL vaccination was myalgia: 46.2%, 37.3% and 25.8% of subjects in Groups A, B and C, respectively. Fever >39.5ºC occurred at <1.0% in all groups.

6.2 Postmarketing Experience

The following adverse events have been spontaneously reported during the postmarketing use of DAPTACEL in the US and other countries. Because these events are reported voluntarily from a population of uncertain size, it may not be possible to reliably estimate their frequency or establish a causal relationship to vaccine exposure.

The following adverse events were included based on one or more of the following factors: severity, frequency of reporting, or strength of evidence for a causal relationship to DAPTACEL.

- Blood and lymphatic disorders
  Lymphadenopathy
- Cardiac disorders
  Cyanosis
- Gastro-intestinal disorders
  Nausea, diarrhea
- General disorders and administration site conditions
  Local reactions: injection site pain, injection site rash, injection site nodule, injection site mass, extensive swelling of injected limb (including swelling that involves adjacent joints).
- Infections and infestations
  Injection site cellulitis, cellulitis, injection site abscess
- Immune system disorders
  Hypersensitivity, allergic reaction, anaphylactic reaction (edema, face edema, swelling face, pruritus, rash generalized) and other types of rash (erythematous, macular, maculo-papular)
- Nervous system disorders
  Convulsions: febrile convulsion, grand mal convulsion, partial seizures
  HHE, hypotonia, somnolence, syncope
- Psychiatric disorders
  Screaming

7 DRUG INTERACTIONS

7.1 Concomitant Administration with Other Vaccines

In clinical trials, DAPTACEL was administered concomitantly with one or more of the following US licensed vaccines: Hib conjugate vaccine, IPV, hepatitis B vaccine, pneumococcal conjugate vaccine, Meningococcal (Groups A, C, Y and W-135) Polysaccharide Diphtheria Toxoid Conjugate vaccine, MMR vaccine, and varicella vaccine. [See Adverse Reactions (6.1) and Clinical Studies (14.4).] When DAPTACEL is given at the same time as another injectable vaccine(s), the vaccines should be administered with different syringes and at different injection sites.

In cases where DAPTACEL and Menactra are to be administered to children 4 through 6 years of age, the two vaccines should be administered concomitantly or Menactra should be administered prior to DAPTACEL. Administration of Menactra one month after DAPTACEL has been shown to reduce meningococcal antibody responses to Menactra. [See Adverse Reactions (6.1) and Clinical Studies (14.4).]

7.2 Immunosuppressive Treatments

Immunosuppressive therapies, including irradiation, antimetabolites, alkylating agents, cytotoxic drugs and corticosteroids (used in greater than physiologic doses), may reduce the immune response to DAPTACEL.

8 USE IN SPECIFIC POPULATIONS

8.4 Pediatric Use

DAPTACEL is not indicated for use in infants below 6 weeks of age or children 7 years of age or older. Safety and effectiveness of DAPTACEL in these age groups have not been established.

11 DESCRIPTION

DAPTACEL is a sterile isotonic suspension of pertussis antigens and diphtheria and tetanus toxoids adsorbed on aluminum phosphate, for intramuscular injection.

Each 0.5 mL dose contains 15 Lf diphtheria toxoid, 5 Lf tetanus toxoid and acellular pertussis antigens [10 mcg detoxified pertussis toxin (PT), 5 mcg filamentous hemagglutinin (FHA), 3 mcg pertactin (PRN), and 5 mcg fimbriae types 2 and 3 (FIM)].

Other ingredients per 0.5 mL dose include 1.5 mg aluminum phosphate (0.33 mg of aluminum) as the adjuvant, ≤5 mcg residual formaldehyde, <50 ng residual glutaraldehyde and 3.3 mg (0.6% v/v) 2-phenoxyethanol (not as a preservative).

The acellular pertussis vaccine components are produced from Bordetella pertussis cultures grown in Stainer-Scholte medium (2) modified by the addition of casamino acids and dimethyl-beta-cyclodextrin. PT, FHA and PRN are isolated separately from the supernatant culture medium. The FIM components are extracted and co-purified from the bacterial cells. The pertussis antigens are purified by sequential filtration, salt-precipitation, ultrafiltration and chromatography. PT is detoxified with glutaraldehyde. FHA is treated with formaldehyde, and the residual aldehydes are removed by ultrafiltration. The individual antigens are adsorbed separately onto aluminum phosphate.

Corynebacterium diphtheriae is grown in modified Mueller's growth medium. (3) After purification by ammonium sulfate fractionation, diphtheria toxin is detoxified with formaldehyde and diafiltered. Clostridium tetani is grown in modified Mueller-Miller casamino acid medium without beef heart infusion. (4) Tetanus toxin is detoxified with formaldehyde and purified by ammonium sulfate fractionation and diafiltration. Diphtheria and tetanus toxoids are individually adsorbed onto aluminum phosphate.

The adsorbed diphtheria, tetanus and acellular pertussis components are combined with aluminum phosphate (as adjuvant), 2-phenoxyethanol (not as a preservative) and water for injection.

Both diphtheria and tetanus toxoids induce at least 2 units of antitoxin per mL in the guinea pig potency test. The potency of the acellular pertussis vaccine components is determined by the antibody response of immunized mice to detoxified PT, FHA, PRN and FIM as measured by enzyme-linked immunosorbent assay (ELISA).

12 CLINICAL PHARMACOLOGY

12.1 Mechanism of Action

Diphtheria

Diphtheria is an acute toxin-mediated disease caused by toxigenic strains of C diphtheriae. Protection against disease is due to the development of neutralizing antibodies to diphtheria toxin. A serum diphtheria antitoxin level of 0.01 IU/mL is the lowest level giving some degree of protection. Antitoxin levels of at least 0.1 IU/mL are generally regarded as protective. (5) Levels of 1.0 IU/mL have been associated with long-term protection. (6)

Tetanus

Tetanus is an acute disease caused by an extremely potent neurotoxin produced by C tetani. Protection against disease is due to the development of neutralizing antibodies to tetanus toxin. A serum tetanus antitoxin level of at least 0.01 IU/mL, measured by neutralization assay is considered the minimum protective level. (5) (7) A tetanus antitoxin level ≥0.1 IU/mL as measured by the ELISA used in clinical studies of DAPTACEL is considered protective.

Pertussis

Pertussis (whooping cough) is a respiratory disease caused by B pertussis. This Gram-negative coccobacillus produces a variety of biologically active components, though their role in either the pathogenesis of, or immunity to, pertussis has not been clearly defined.

13 NONCLINICAL TOXICOLOGY

13.1 Carcinogenesis, Mutagenesis, Impairment of Fertility

DAPTACEL has not been evaluated for carcinogenic or mutagenic potential or impairment of fertility.

14 CLINICAL STUDIES

14.1 Diphtheria

In a US study in which children received 4 doses of DAPTACEL at 2, 4, 6 and 15-17 months of age, after the third dose, 100% (N = 1,099) achieved diphtheria antitoxin levels of ≥0.01 IU/mL and 98.5% achieved diphtheria antitoxin levels of ≥0.10 IU/mL. Among a random subset of children who received the fourth dose of DAPTACEL at 15-16 months of age, 96.5% (N = 659) achieved diphtheria antitoxin levels of ≥1.0 IU/mL after the fourth dose.

14.2 Tetanus

In a US study in which children received 4 doses of DAPTACEL at 2, 4, 6 and 15-17 months of age, after the third dose, 100% (N = 1,037) achieved tetanus antitoxin levels of ≥0.10 IU/mL. Among a random subset of children who received the fourth dose of DAPTACEL at 15-16 months of age, 98.8% (N = 681) achieved tetanus antitoxin levels of ≥1.0 IU/mL after the fourth dose.

14.3 Pertussis

A randomized, double-blinded, placebo-controlled efficacy and safety study was conducted in Sweden during 1992-1995 (Sweden I Efficacy Trial) under the sponsorship of the National Institute of Allergy and Infectious Diseases. A total of 9,829 infants received 1 of 4 vaccines: DAPTACEL (N = 2,587); another investigational acellular pertussis vaccine (N = 2,566); whole-cell pertussis DTP vaccine (N = 2,102); or DT vaccine as placebo (Swedish National Bacteriological Laboratory, N = 2,574). Infants were immunized at 2, 4 and 6 months of age. The mean length of follow-up was 2 years after the third dose of vaccine. The protective efficacy of DAPTACEL against pertussis after 3 doses using the World Health Organization (WHO) case definition (≥21 consecutive days of paroxysmal cough with culture or serologic confirmation or epidemiologic link to a confirmed case) was 84.9% (95% confidence interval [CI] 80.1 to 88.6). The protective efficacy of DAPTACEL against mild pertussis (≥1 day of cough with laboratory confirmation) was 77.9% (95% CI 72.6 to 82.2). Protection against pertussis by DAPTACEL was sustained for the 2-year follow-up period.

In order to assess the antibody response to the pertussis antigens of DAPTACEL in the US population, 2 lots of DAPTACEL, including the lot used in the Sweden I Efficacy Trial, were administered to US infants in the US Bridging Study. In this study, antibody responses following 3 doses of DAPTACEL given to US children at 2, 4 and 6 months of age were compared to those from a subset of the infants enrolled in the Sweden I Efficacy Trial. Assays were performed in parallel on the available sera from the US and Swedish infants. Antibody responses to all the antigens were similar except for those to the PRN component. For both lots of DAPTACEL, the geometric mean concentration (GMC) and percent response to PRN in US infants (Lot 006, N = 107; Lot 009, N = 108) were significantly lower after 3 doses of vaccine than in Swedish infants (N = 83). In separate US and Canadian studies in which children received DAPTACEL at 2, 4 and 6 months of age, with a fourth dose at either 17-20 months (Canadian study) or 15-16 months (random subset from US study) of age, antibody responses to each pertussis antigen following the fourth dose (Canadian study N = 275; US study N = 237-347) were at least as high as those seen in the Swedish infants after 3 doses. While a serologic correlate of protection for pertussis has not been established, the antibody response to all antigens in North American infants after 4 doses of DAPTACEL at 2, 4, 6 and 15-20 months of age was comparable to that achieved in Swedish infants in whom efficacy was demonstrated after 3 doses of DAPTACEL at 2, 4 and 6 months of age.

In the US Study 005, infants were randomized to receive 3 doses of VAXELIS at 2, 4, and 6 months of age and DAPTACEL and PedvaxHIB [Haemophilus b Conjugate Vaccine (Meningococcal Protein Conjugate)] at 15 months of age, or Control group vaccines (3 doses of Pentacel vaccine at 2, 4, and 6 months of age + RECOMBIVAX HB [Hepatitis B Vaccine (Recombinant)] at 2 and 6 months of age and DAPTACEL and ActHIB [Haemophilus b Conjugate Vaccine (Tetanus Toxoid Conjugate)] at 15 months of age). All subjects received concomitant Prevnar 13 (Pneumococcal 13-valent Conjugate Vaccine [Diphtheria CRM197 Protein]) at 2, 4, 6, and 15 months of age. To complete the 4-dose pertussis primary vaccination series, participants in both groups received DAPTACEL at 15 months of age and were evaluated for immune responses to pertussis antigens one month later.

The non-inferiority criteria for vaccine response rates and GMCs for all pertussis antigens were met following the fourth dose. (8)

14.4 Concomitantly Administered Vaccines

In the US Bridging study, DAPTACEL was given concomitantly with Hib conjugate vaccine (Sanofi Pasteur SA) according to local practices. Anti-PRP immune response was evaluated in 261 infants who received 3 doses of Hib conjugate vaccine. One month after the third dose, 96.9% achieved anti-PRP antibody levels of at least 0.15 mcg/mL and 82.7% achieved antibody levels of at least 1.0 mcg/mL.

In the US study in which infants received DAPTACEL concomitantly with Hib conjugate (tetanus toxoid conjugate) vaccine, IPV, 7-valent pneumococcal conjugate vaccine, and hepatitis B vaccine [see Adverse Reactions (6.1)], at 7 months of age, 100.0% of subjects (N = 1,050-1,097) had protective neutralizing antibody levels (≥1:8 1/dil) for poliovirus types 1, 2 and 3; and 92.4% (N = 998) achieved anti-hepatitis B surface antigen levels ≥10.0 mIU/mL. Although there is no established serologic correlate of protection for any of the pneumococcal serotypes, at 7 months of age 91.3%-98.9% (N = 1,027-1,029) achieved anti-pneumococcal polysaccharide levels ≥0.5 mcg/mL for serotypes 4, 9V, 14, 18C, 19F and 23F and 80.7% (N = 1,027) achieved an anti-pneumococcal polysaccharide level ≥0.5 mcg/mL for serotype 6B. The mumps seroresponse rate was lower when DAPTACEL was administered concomitantly (86.6%; N = 307) vs. non-concomitantly (90.1%; N = 312) with the first dose of MMR vaccine [upper limit of 90% confidence interval for difference in rates (non-concomitant minus concomitant) >5%]. There was no evidence for interference in the immune response to the measles, rubella, and varicella antigens or to the fourth dose of the 7-valent pneumococcal conjugate vaccine with concomitant administration of DAPTACEL.

In a randomized, parallel-group, US multi-center clinical trial conducted in children 4 through 6 years of age, DAPTACEL was administered as follows: concomitantly with IPV (Sanofi Pasteur SA) followed 30 days later by Menactra [Group A]; concomitantly with Menactra followed 30 days later by IPV [Group B]; or 30 days after concomitant administration of Menactra and IPV [Group C]. Sera were obtained approximately 30 days after each respective vaccination. When DAPTACEL was administered concomitantly with Menactra [Group B], antibody responses to PT, FHA and PRN (GMC), tetanus (% participants with antibody concentrations ≥1.0 IU/mL), and diphtheria (%participants with antibody concentrations ≥1.0 IU/mL) were non-inferior to those observed when DAPTACEL (and IPV) were administered [Group A]. The anti-FIM GMCs were marginally lower when DAPTACEL and Menactra were administered concomitantly but the clinical significance is unknown because there are no established serological correlates of protection for pertussis. When DAPTACEL (and IPV) were administered 30 days prior to Menactra [Group A], significantly lower serum-bactericidal assay-human complement (SBA-H) GMTs to all 4 meningococcal serogroups were observed compared to when Menactra (and IPV) were administered 30 days prior to DAPTACEL [Group C]. When DAPTACEL was administered concomitantly with Menactra [Group B], SBA-H GMTs to meningococcal serogroups A, C, and W-135 were non-inferior to those observed when Menactra (and IPV) were administered [Group C]. The non-inferiority criterion was marginally missed for meningococcal serogroup Y. [See Drug Interactions (7.1).]

15 REFERENCES

1 Stratton KR, et al. editors. Adverse events associated with childhood vaccines; evidence bearing on causality. Washington D.C.: National Academy Press. 1994. p. 67-117.
2 Stainer DW, Scholte MJ. A simple chemically defined medium for the production of phase I Bordetella pertussis. J Gen Microbiol 1970;63:211-20.
3 Stainer DW. Production of diphtheria toxin. In: Manclark CR, editor. Proceedings of an informal consultation on the World Health Organization requirements for diphtheria, tetanus, pertussis and combined vaccines. United States Public Health Service, Bethesda, MD. DHHS 91-1174. 1991. p. 7-11.
4 Mueller JH, Miller PA. Variable factors influencing the production of tetanus toxin. J Bacteriol 1954;67(3):271-7.
5 Department of Health and Human Services, Food and Drug Administration. Biological products; bacterial vaccines and toxoids; implementation of efficacy review; proposed rule. Federal Register 1985;50(240):51002-117.
6 Wharton M, et al. Diphtheria Toxoid. In: Plotkin SA, Orenstein WA, editors. Vaccines. 4th ed. Philadelphia, PA: W. B. Saunders 2004 p. 211-28.
7 Wassilak SGF, et al. Tetanus Toxoid. In: Plotkin SA, Orenstein WA, editors. Vaccines. 4th ed. Philadelphia, PA: W. B. Saunders 2004 p. 745-81.
8 VAXELIS® [full prescribing information]. Toronto, ON: MSP Vaccine Company.

16 HOW SUPPLIED/STORAGE AND HANDLING

The vial stopper for this product is not made with natural rubber latex.

DAPTACEL is supplied in a single-dose vial (NDC No. 49281-286-58):

in packages of 1 vial: NDC No. 49281-286-01;

in packages of 5 vials: NDC No. 49281-286-05;

in packages of 10 vials: NDC No. 49281-286-10.

STORAGE AND HANDLING

DAPTACEL should be stored at 2° to 8°C (35° to 46°F). DO NOT FREEZE. Product which has been exposed to freezing should not be used. Do not use after expiration date shown on the label.

17 PATIENT COUNSELING INFORMATION

Inform the parent or guardian of the following:

- The potential benefits and risks of immunization with DAPTACEL.
- The common adverse reactions that have occurred following administration of DAPTACEL or other vaccines containing similar components.
- Other adverse reactions can occur. Call healthcare provider with any adverse reactions of concern.

Provide the Vaccine Information Statements (VIS), which are required by the National Childhood Vaccine Injury Act of 1986.

Manufactured by:
Sanofi Pasteur Limited
Toronto Ontario Canada

Distributed by:
Sanofi Pasteur Inc.
Swiftwater PA 18370 USA

US Patents: 4500639, 4687738, 4784589, 4997915, 5444159, 5667787, 5877298.

DAPTACEL® is a registered trademark of Sanofi, its affiliates and subsidiaries.

R13-0823 USA

PRINCIPAL DISPLAY PANEL - 0.5 mL Vial Label

6 wks - 6 yrs
DTaP

NDC 49281-286-58

Diphtheria and Tetanus
Toxoids and Acellular
Pertussis Vaccine
Adsorbed

DAPTACEL®
Rx only

Single-dose (0.5 mL) IM only
Sanofi Pasteur Limited

PRINCIPAL DISPLAY PANEL - 0.5 mL Vial Package

NDC 49281-286-10
DTaP

Diphtheria and Tetanus
Toxoids and Acellular Pertussis
Vaccine Adsorbed

DAPTACEL®

Rx only

Dose: 0.5 mL intramuscularly.
For children 6 weeks through 6 years of age.

10 single-dose vials 0.5 mL

sanofi